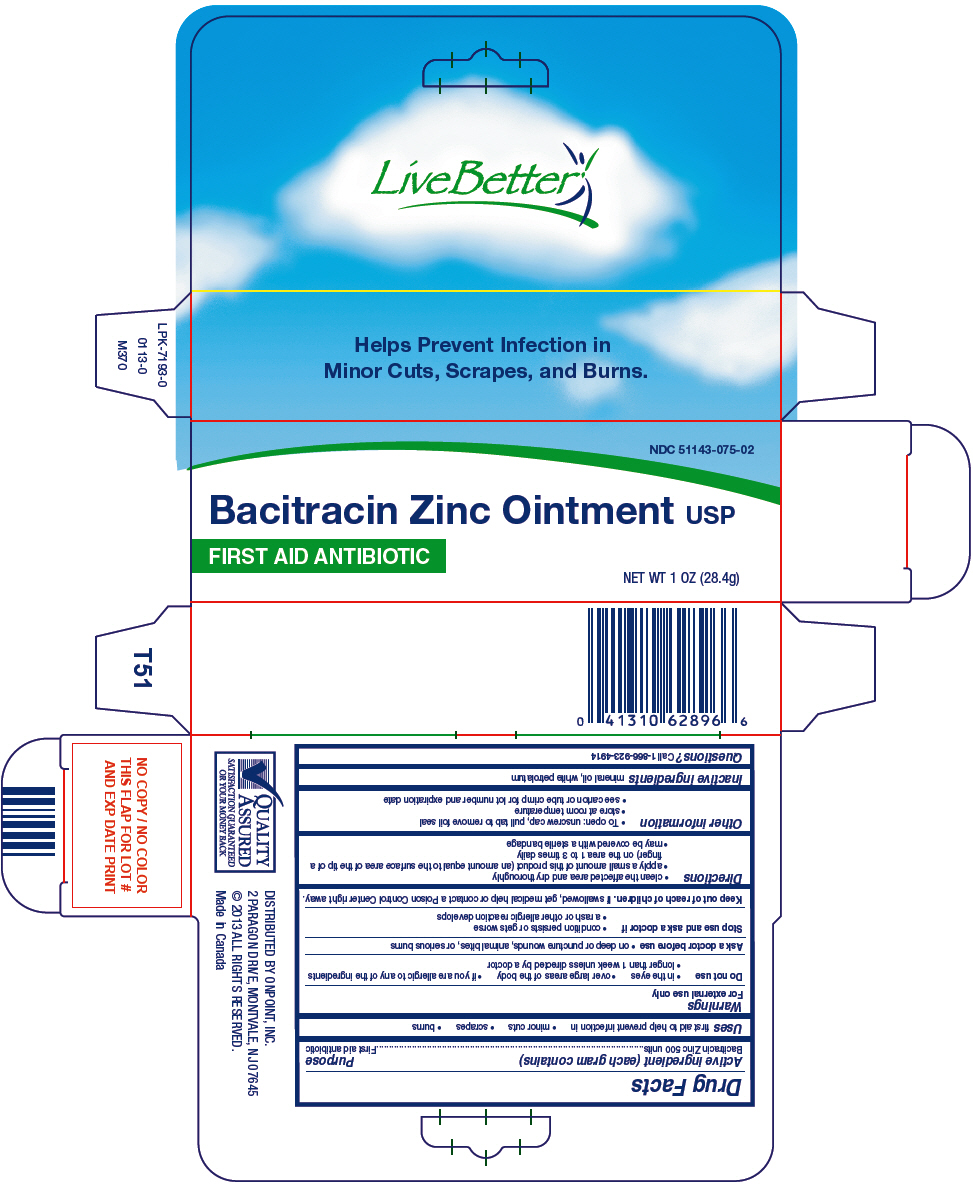 DRUG LABEL: Live Better

NDC: 51143-075 | Form: OINTMENT
Manufacturer: The Great Atlantic & Pacific Tea Company
Category: otc | Type: HUMAN OTC DRUG LABEL
Date: 20250711

ACTIVE INGREDIENTS: BACITRACIN ZINC 500 [iU]/1 g
INACTIVE INGREDIENTS: MINERAL OIL; PETROLATUM

Live Better
Bacitracin Zinc

Active ingredient (each gram contains)

Bacitracin Zinc 500 units

Purpose

First aid antibiotic

Uses

first aid to help prevent infection in

- minor cuts
- scrapes
- burns

Warnings

For external use only

Do not use

- in the eyes
- over large areas of the body
- if you are allergic to any of the ingredients
- longer than 1 week unless directed by a doctor

Ask a doctor before use

- on deep or puncture wounds, animal bites, or serious burns

Stop use and ask a doctor if

- condition persists or gets worse
- a rash or other allergic reaction develops

Keep out of reach of children.If swallowed, get medical help or contact a Poison Control Center right away.

Directions

- clean the affected area and dry thoroughly
- apply a small amount of this product (an amount equal to the surface area of the tip of a finger) on the area 1 to 3 times daily
- may be covered with a sterile bandage

Other information

- To open: unscrew cap, pull tab to remove foil seal
- store at room temperature
- see carton or tube crimp for lot number and expiration date

Inactive ingredients

mineral oil, white petrolatum

Questions?

Call 1-866-923-4914

DISTRIBUTED BY ONPOINT, INC.
2 PARAGON DRIVE, MONTVALE, NJ 07645

PRINCIPAL DISPLAY PANEL - 28.4 g Tube Carton

NDC 51143-075-02

Bacitracin Zinc Ointment USP

FIRST AID ANTIBIOTIC

NET WT 1 OZ (28.4g)